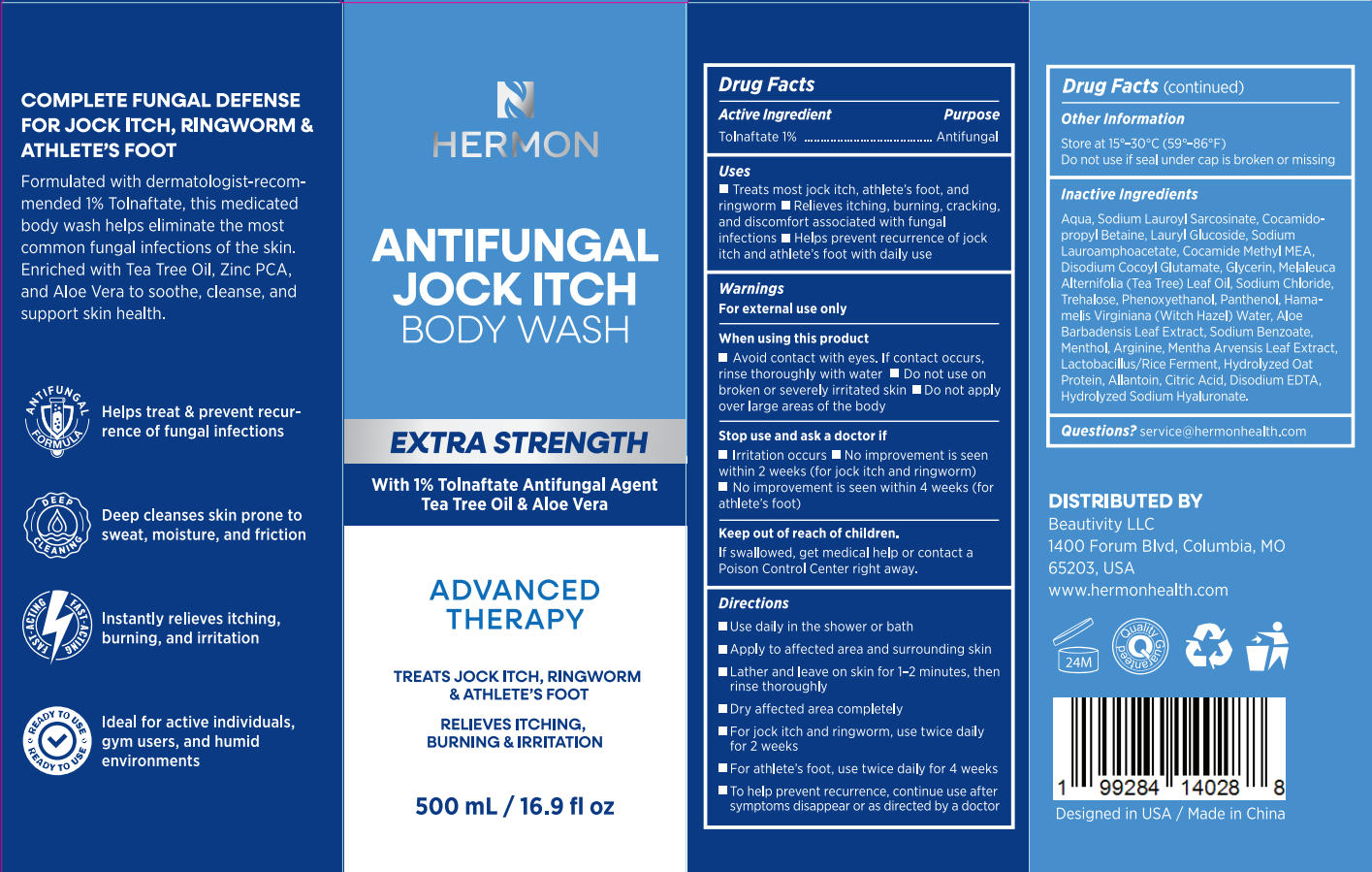 DRUG LABEL: Hermon Antifungal Jock Itch Body Wash
NDC: 85398-016 | Form: GEL
Manufacturer: Beautivity LLC
Category: otc | Type: HUMAN OTC DRUG LABEL
Date: 20251008

ACTIVE INGREDIENTS: TOLNAFTATE 5 g/500 g
INACTIVE INGREDIENTS: HAMAMELIS VIRGINIANA (WITCH HAZEL) LEAF WATER; ALOE BARBADENSIS LEAF JUICE; TREHALOSE; HYDROLYZED SOY PROTEIN (ENZYMATIC; 2000 MW); SODIUM CHLORIDE; COCAMIDOPROPYL BETAINE; AQUA; MELALEUCA ALTERNIFOLIA (TEA TREE) LEAF OIL; COCAMIDE METHYL MEA; PANTHENOL; SODIUM HYALURONATE; SODIUM LAUROYL SARCOSINATE; PHENOXYETHANOL; CALCIUM DISODIUM EDTA; GLYCERIN; ARGININE; CITRIC ACID; ALLANTOIN; DISODIUM COCOYL GLUTAMATE; LACTOBACILLUS; SODIUM BENZOATE; MENTHA ARVENSIS LEAF; MENTHOL; LAURYL GLUCOSIDE; SODIUM LAUROAMPHOACETATE

Initial Drug Listing - Hermon Antifungal Jock Itch Body Wash

ACTIVE INGREDIENT

Tolnaftate 1%

PURPOSE

Antifungal

DOSAGE AND ADMINISTRATION

- Treats most jock itch, athlete's foot, and ringworm
- Relieves itching, burning, cracking,and discomfort associated with fungal infections
- Helps prevent recurrence of jock itch and athlete's foot with daily use

WARNINGS

For external use only

WHEN USING

- Avoid contact with eyes. lf contact occurs, rinse thoroughly with water
- Do not use onbroken or severely irritated skin
- Do not apply over large areas of the body

ASK DOCTOR

- lrritation occurs
- No improvement is seen within 2 weeks (for jock itch and ringworm)
- No improvement is seen within 4 weeks (for athlete's foot)

KEEP OUT OF REACH OF CHILDREN

If swallowed, get medical help or contact aPoison Control Center right away.

INDICATIONS AND USAGE

- Use daily in the shower or bath
- Apply to affected area and surrounding skin
- Lather and leave on skin for 1-2 minutes, thenrinse thoroughly
- Dry affected area completely
- For jock itch and ringworm, use twice daily for 2 weeks
- For athlete's foot, use twice daily for 4 weeks
- To help prevent recurrence, continue use after symptoms disappear or as directed by a doctor

OTHER SAFETY INFORMATION

Store at 15°-30°C(59°-86°F)

Do not use if seal under cap is broken or missing

INACTIVE INGREDIENT

Aqua, Sodium Lauroyl Sarcosinate, Cocamidopropyl Betaine, Lauryl Glucoside, Sodium Lauroamphoacetate, Cocamide Methyl MEA,Disodium Cocoyl Glutamate, Glycerin, Melaleuca Alternifolia (Tea Tree) Leaf Oil, Sodium Chloride,Trehalose, Phenoxyethanol, Panthenol, Hamamelis virginiana (Witch Hazel) Water, Aloe Barbadensis Leaf Extract, Sodium Benzoate,Menthol, Arginine, Mentha Arvensis Leaf Extract, Lactobacillus/Rice Ferment, Hydrolyzed OatProtein, Allantoin, Citric Acid, Disodium EDTA,Hydrolyzed Sodium Hyaluronate.

QUESTIONS

service@hermonhealth.com